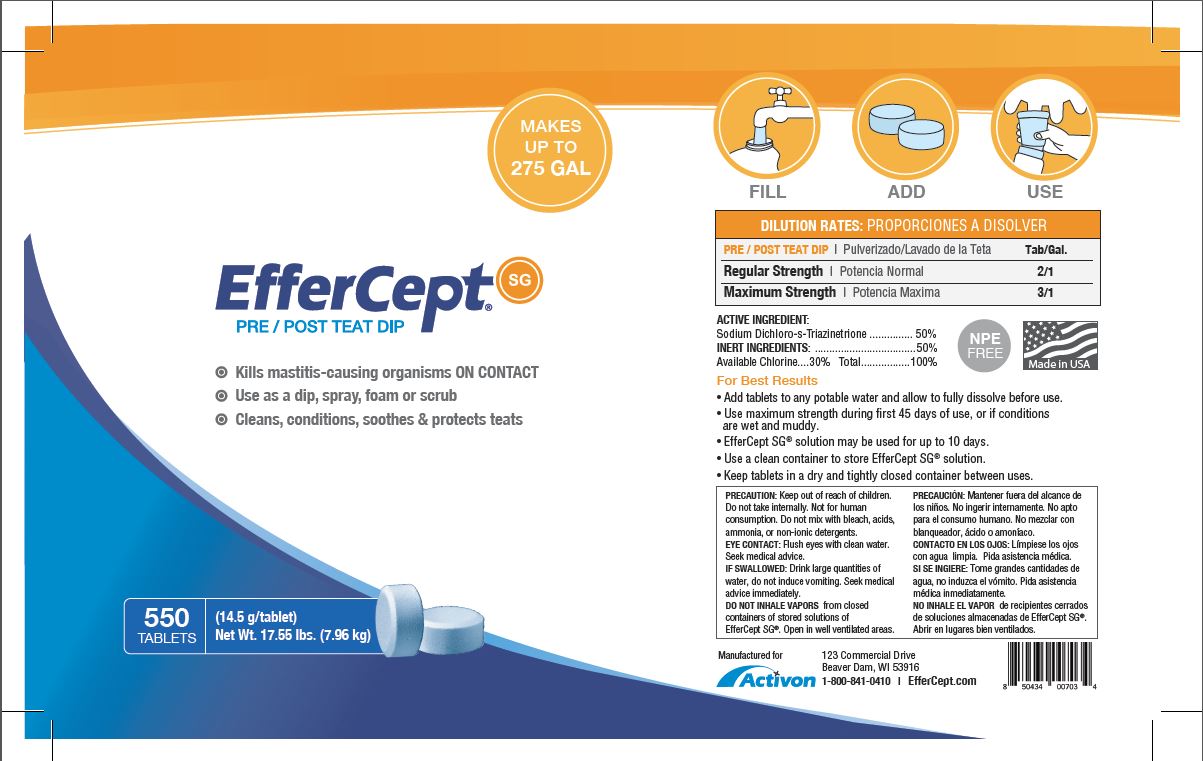 DRUG LABEL: EfferCept SG
NDC: 14925-302 | Form: FOR SOLUTION
Manufacturer: Activon
Category: animal | Type: OTC ANIMAL DRUG LABEL
Date: 20221219

ACTIVE INGREDIENTS: TROCLOSENE SODIUM 7.25 g/14.5 g

Package Labeling

DOSAGE AND ADMINISTRATION

DILUTION RATES

PRE/POST TEAT DIP Tab/Gal.

Regular Strength 2/1

Maximum Strength 3/1

ACTIVE INGREDIENT:

Sodium Dichloro-s-Triazinetrione................50%

INERT INGREDIENTS:.........................50%

Available Chlorine....30% Total...............100%

STORAGE AND HANDLING

For Best Results

- Add tablets to any potable water and allow to fully dissolve before use.
- Use maximum strength during first 45 days of use, or if conditions are wet and muddy.
- For extra foaming of teat conditioning, add SoftGuard to solution.
- EfferCept SG solution may be used for up to 10 days.
- Use a clean container to store EfferCept SG solution.
- Keep tablets in a dry and tightly closed container between uses.

PRECAUTIONS

PRECAUTION: Keep out of reach of children. Do not take Internally. Not for human consumption. Do not mix with bleach, acids, ammonia, or non-ionic detergents.

EYE CONTACT: Flush eyes with clean water. Seek medical advice.

IF SWALLOWED: Drink large quantities of water, do not induce vomiting. Seek medical advice immediately.

DO NOT INHALE VAPORS from closed containers of stored solutions of EfferCept SG. Open in well ventilated areas.

PACKAGE LABEL

FILL ADD USE

MAKES UP TO XX GAL

EfferCept SG

PRE/ POST TEAT DIP

Kills mastitis-causing organisms ON CONTACT

Use as a dip, spray, foam or scrub

Cleans, conditions, soothes and protects teats

550 TABLETS

(14.5 g/tablet)

Net WT. 17.55 lbs. (7.96 kg)